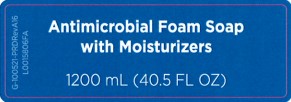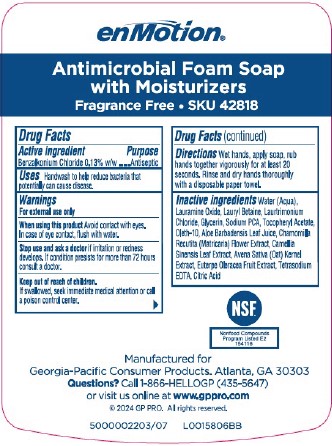 DRUG LABEL: enMotion Antimicrobial

NDC: 54622-703 | Form: SOAP
Manufacturer: Georgia-Pacific Consumer Products LP
Category: otc | Type: HUMAN OTC DRUG LABEL
Date: 20260204

ACTIVE INGREDIENTS: BENZALKONIUM CHLORIDE 1.3 mg/1 mL
INACTIVE INGREDIENTS: WATER; LAURAMINE OXIDE; LAURYL BETAINE; LAURTRIMONIUM CHLORIDE; GLYCERIN; SODIUM PYRROLIDONE CARBOXYLATE; .ALPHA.-TOCOPHEROL ACETATE; OLETH-10; ALOE VERA LEAF JUICE; MATRICARIA CHAMOMILLA WHOLE; GREEN TEA LEAF; OAT; ACAI; EDETATE SODIUM; CITRIC ACID MONOHYDRATE

enMotion 700.001/700AC
Antimicrobial Soap - Dye Free, Fragrance Free

Claims

enMotion

Antimicrobial Foam Soap

with Moisturizers

Fragrance Free • SKU 42818

Active ingredient

Benzalkonium Chloride 0.13% w/w

Purpose

Antiseptic

Uses

Handwash to help reduce bacteria that potentially can cause disease.

Warnings

For external use only

When using this product

Avoid contact with eyes. In case of eye contact, flush with water.

Stop use and ask a doctor

if irritation or redness develops. If condition persists for more than 72 hours consult a doctor.

Keep out of reach of children.

If swallowed, seek immediate medical attention or call a poison control center.

Directions

Wet hands, apply soap, rub hand together vigorously for at least 20 seconds. Rinse and dry hand thoroughly with a disposable paper towel.

Inactive ingredients

Water (Aqua), Lauramine Oxide, Lauryl Betaine, Laurtrimonium Chloride, Glycerin, Sodium PCA, Tocopheryl Acetate, Oleth-10, Aloe Barbadensis Leaf Juice, Chamomilla Recutita (Matricaria) Flower Extract, Camellia Sinensis Leaf Extract, Avena Sativa (oat) Kernel Extract, Euterpe Oleracea Fruit Extract, Tetrasodium EDTA, Citric Acid

Adverse reaction

NSF

Nonfood Compounds Program Listed E2 154116

Manufactured for Georgia-Pacific Consumer Products. Atlanta, GA 30303

Questions? Call 1-866-HELLOGP (435-5647)

or visit us online at www.gppro.com

2024 GP PRO. All rights reserved.

principal display panel

Antimicrobial Foam Soap with Moisturizers

1200 mL (40.5 FL OZ)